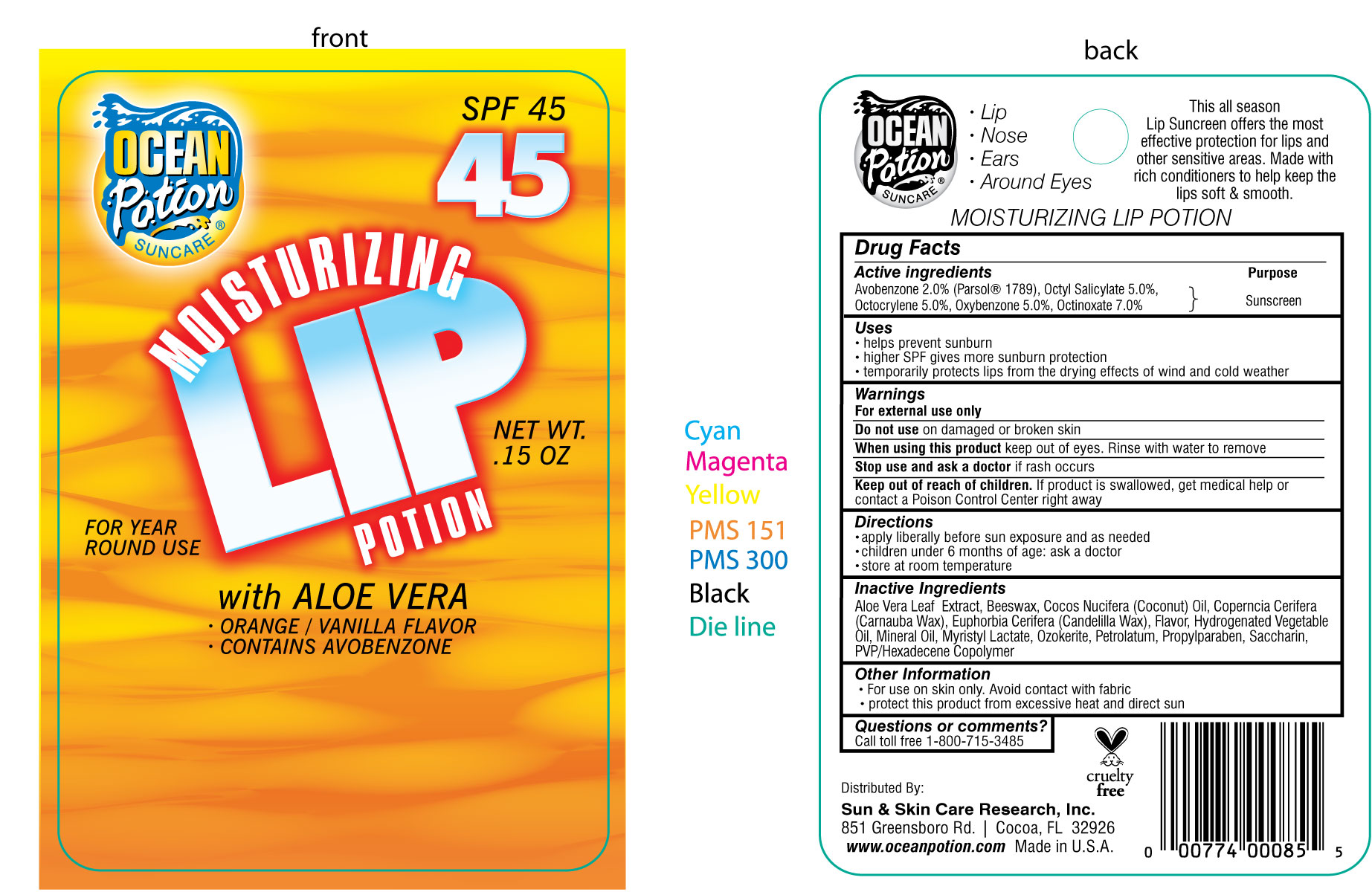 DRUG LABEL: Ocean Potion Moisturizing Lip Potion 45
NDC: 62802-085 | Form: LIPSTICK
Manufacturer: Sun & Skin Care Research, LLC
Category: otc | Type: HUMAN OTC DRUG LABEL
Date: 20120518

ACTIVE INGREDIENTS: OCTINOXATE 7.5 g/100 g; OCTISALATE 5 g/100 g; OXYBENZONE  5.0 g/100 g; OCTOCRYLENE 5.0 g/100 g; AVOBENZONE 2 g/100 g
INACTIVE INGREDIENTS: ALOE VERA LEAF; YELLOW WAX; COCONUT OIL; CARNAUBA WAX; CANDELILLA WAX; CORN OIL; MINERAL OIL; MYRISTYL LACTATE; CERESIN; PETROLATUM; PROPYLPARABEN; SACCHARIN

Drug Facts

Active Ingredients

Avobenzone: 2%
Octinoxate: 7%
Octisalate: 5%
Octocrylene: 5%
Oxybenzone: 5%

Purpose

Sunscreen

Uses

- helps prevent sunburn
- higher SPF gives more sunburn protection
- temporarily protects lips from the drying effects of wind and cold weather

Warnings

For external use only. Do not use on damaged or broken skin. Stop use and ask a doctor if rash occurs. When using this product keep out of eyes. Rinse with water to remove. Keep out of the reach of children. If swallowed, get medical help or contact a Poison Control Center right away.

Directions

- apply liberally before sun exposure and as needed
- children under 6 months of age: ask a doctor
- store at room temperature

Other Information

- For use on skin only
- Avoid contact with fabric
- Protect this product from excessive heat and direct sun